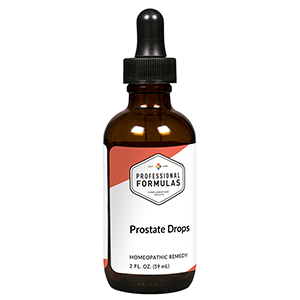 DRUG LABEL: Prostate Drops
NDC: 63083-2052 | Form: LIQUID
Manufacturer: Professional Complementary Health Formulas
Category: homeopathic | Type: HUMAN OTC DRUG LABEL
Date: 20190815

ACTIVE INGREDIENTS: PYGEUM 2 [hp_X]/59 mL; SAW PALMETTO 2 [hp_X]/59 mL; BEE POLLEN 3 [hp_X]/59 mL; ZINC 3 [hp_X]/59 mL; BOS TAURUS PROSTATE GLAND 6 [hp_X]/59 mL; PULSATILLA MONTANA WHOLE 12 [hp_X]/59 mL; BOVINE TUBERCULIN 30 [hp_X]/59 mL
INACTIVE INGREDIENTS: ALCOHOL; WATER

C52

ACTIVE INGREDIENTS

Pygeum africanum 2X
Sabal serrulata 2X
Bee pollen 3X
Zincum metallicum 3X
Prostate 6X
Pulsatilla 12X
Tuberculinum 30X, 100X

QUESTIONS

Professional Formulas

PO Box 2034 Lake Oswego, OR 97035

INDICATIONS

For the temporary relief of difficult urination, excessive or frequent urge to urinate, or mild discomfort in the groin or genitals.*

PURPOSE

*Claims based on traditional homeopathic practice, not accepted medical evidence. Not FDA evaluated.

WARNINGS

Consult a doctor if condition worsens or if symptoms persist. Keep out of the reach of children. In case of overdose, get medical help or contact a poison control center right away. If pregnant or breastfeeding, ask a healthcare professional before use.

Keep out of the reach of children.

PREGNANCY OR BREAST FEEDING

If pregnant or breastfeeding, ask a healthcare professional before use.

DIRECTIONS

Place drops under tongue 30 minutes before/after meals. Adults and children 12 years and over: Take 10 drops up to 3 times per day. Consult a physician for use in children under 12 years of age. Not intended for use in infants.

OTHER INFORMATION

Tamper resistant. If seal is broken, do not use. After opening, close container tightly and store at room temperature away from heat.

INACTIVE INGREDIENTS

20% ethanol, purified water.

LABEL

Est 1985

Professional Formulas

Complementary Health

Prostate Drops

Homeopathic Remedy

2 FL. OZ. (59 mL)